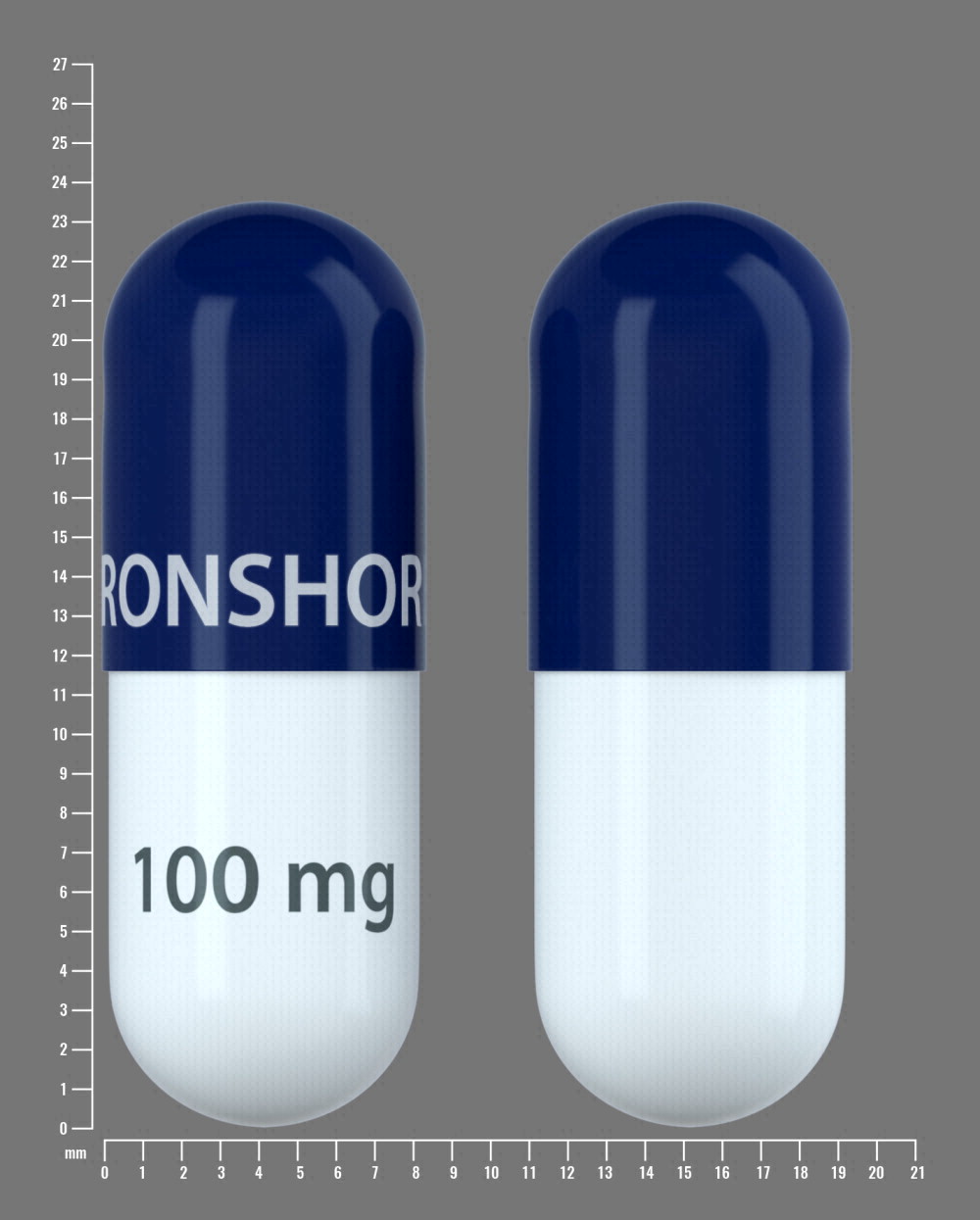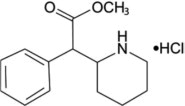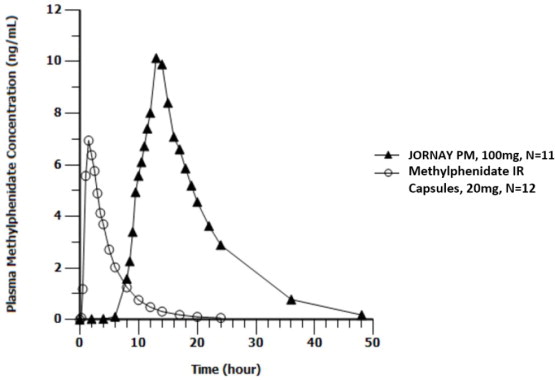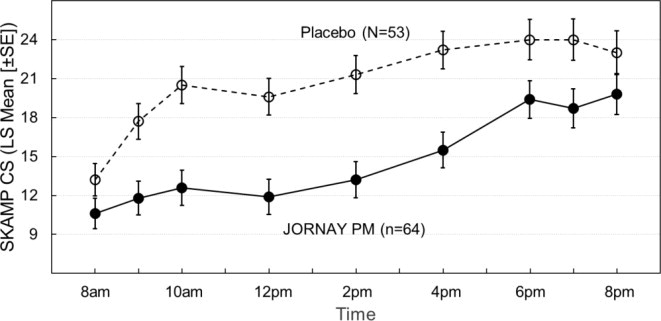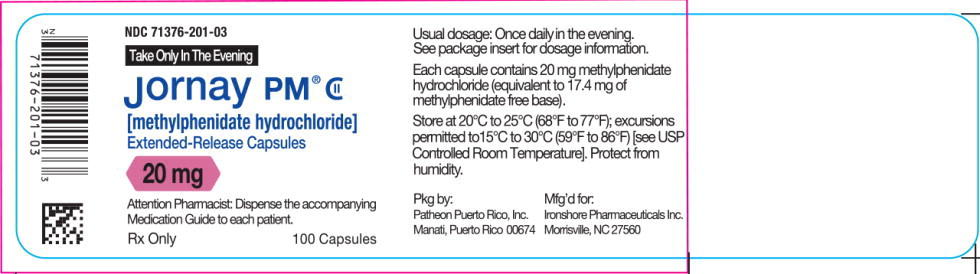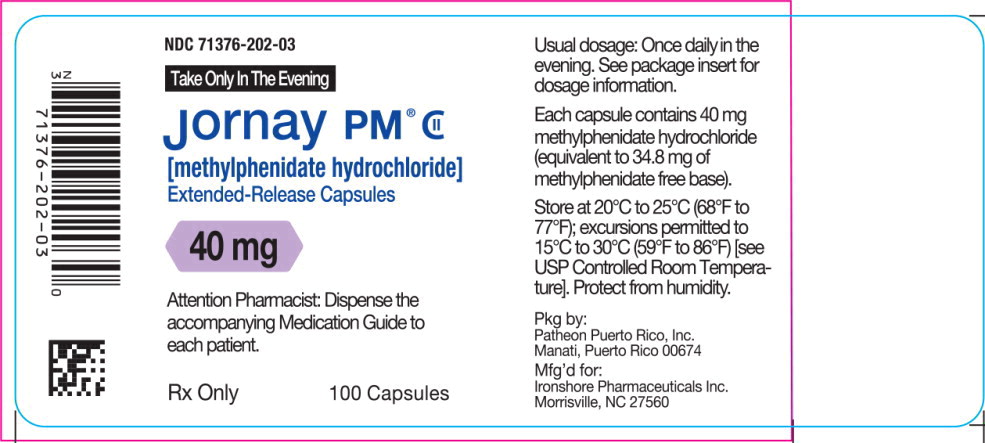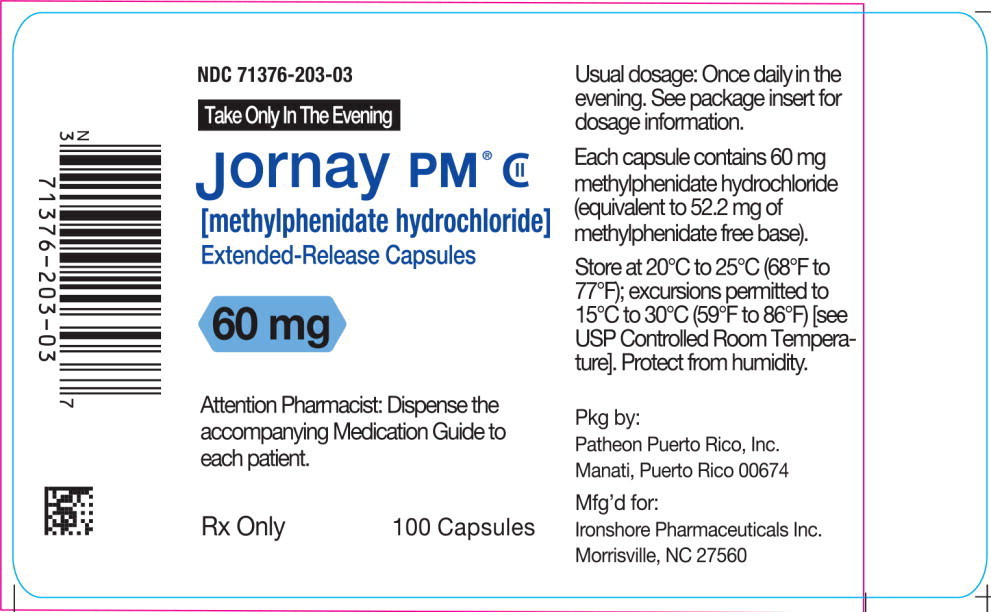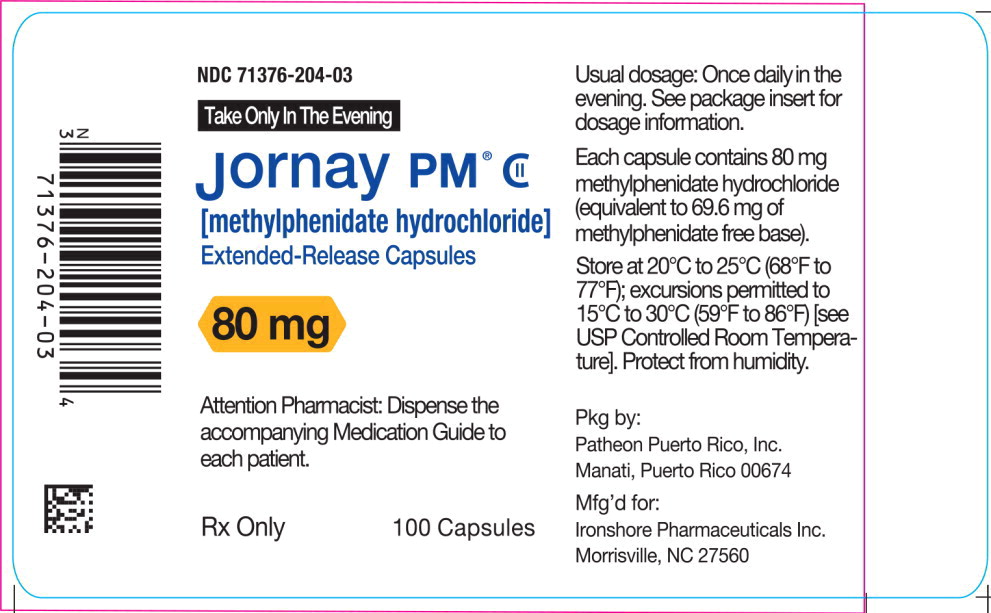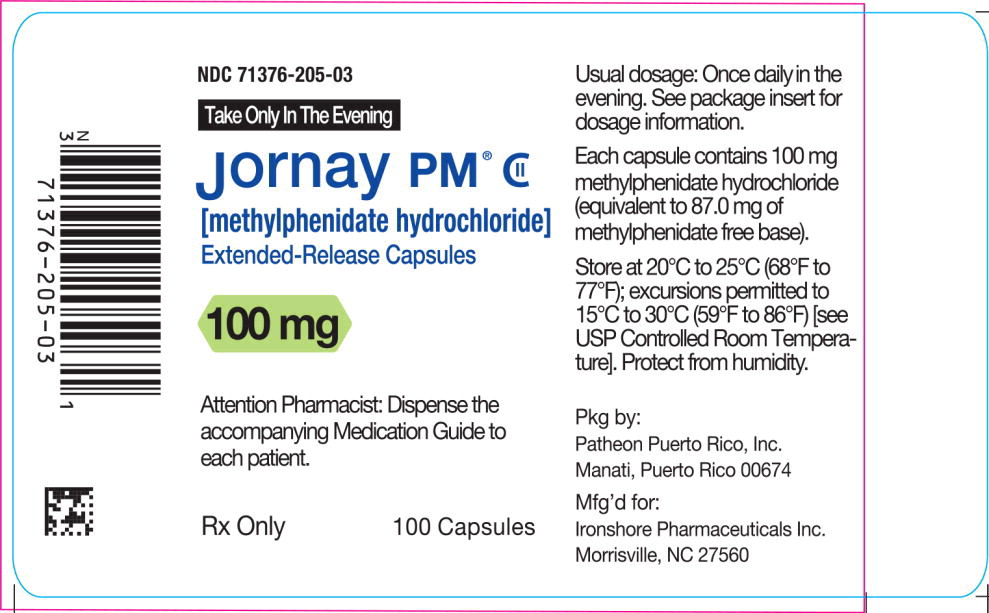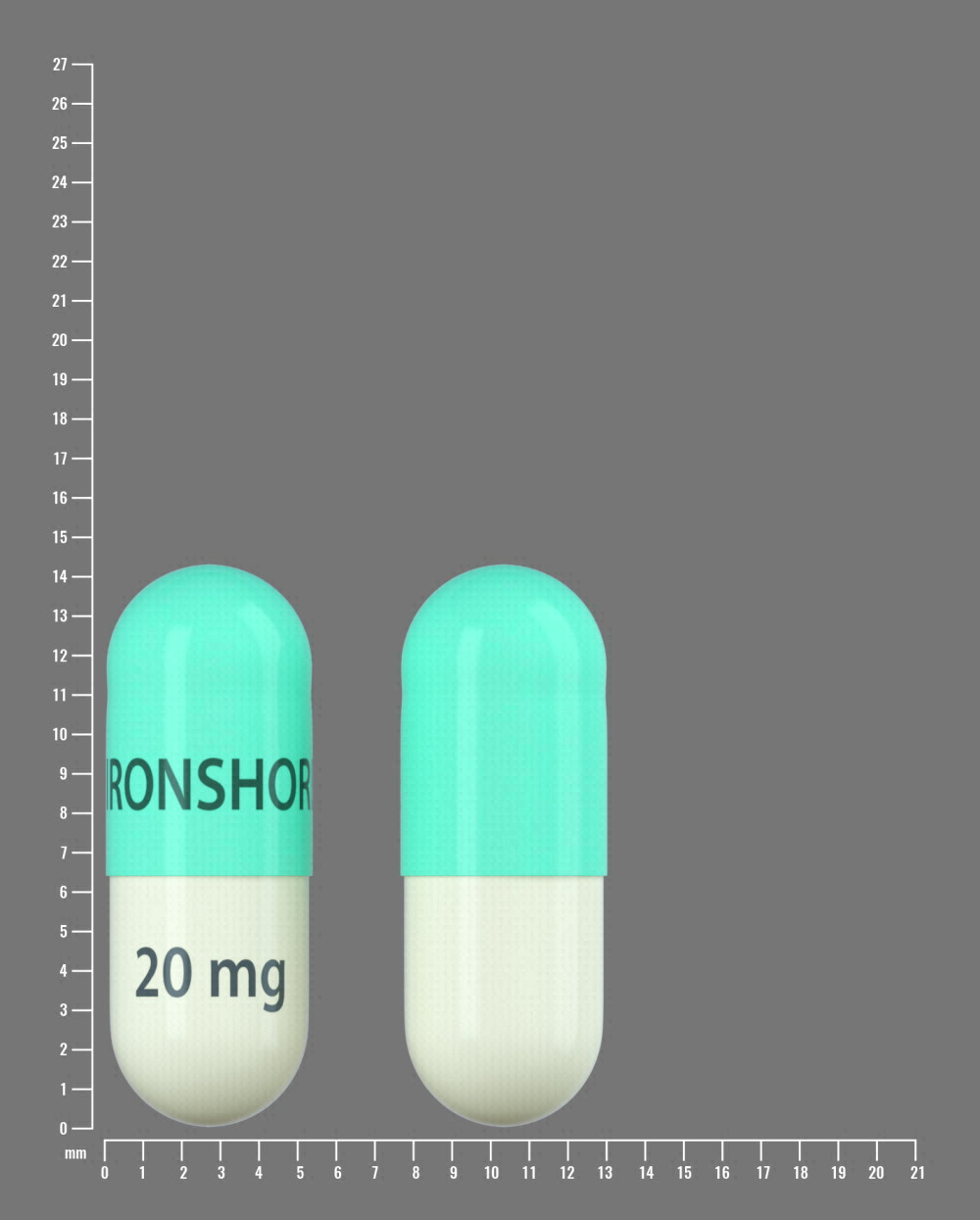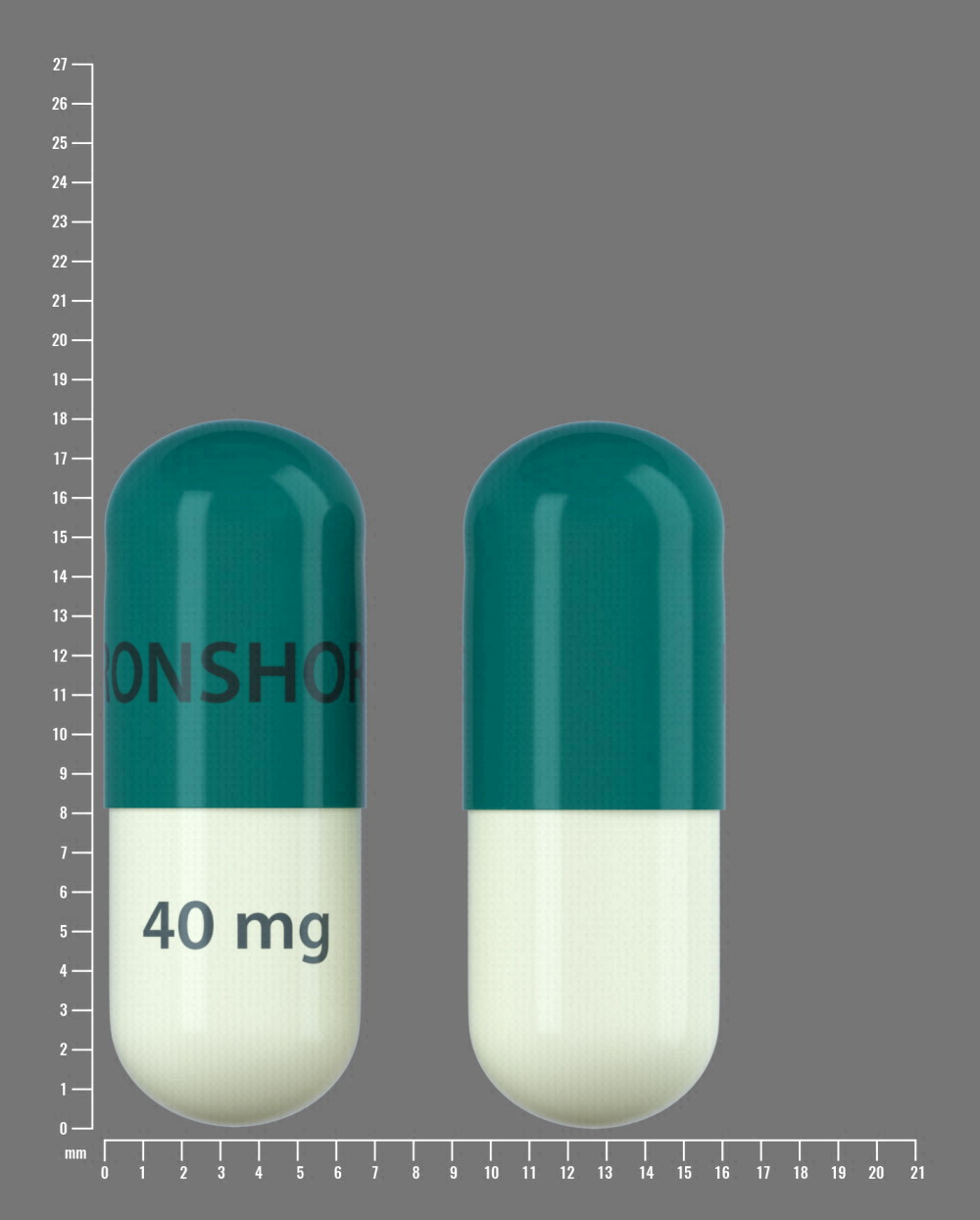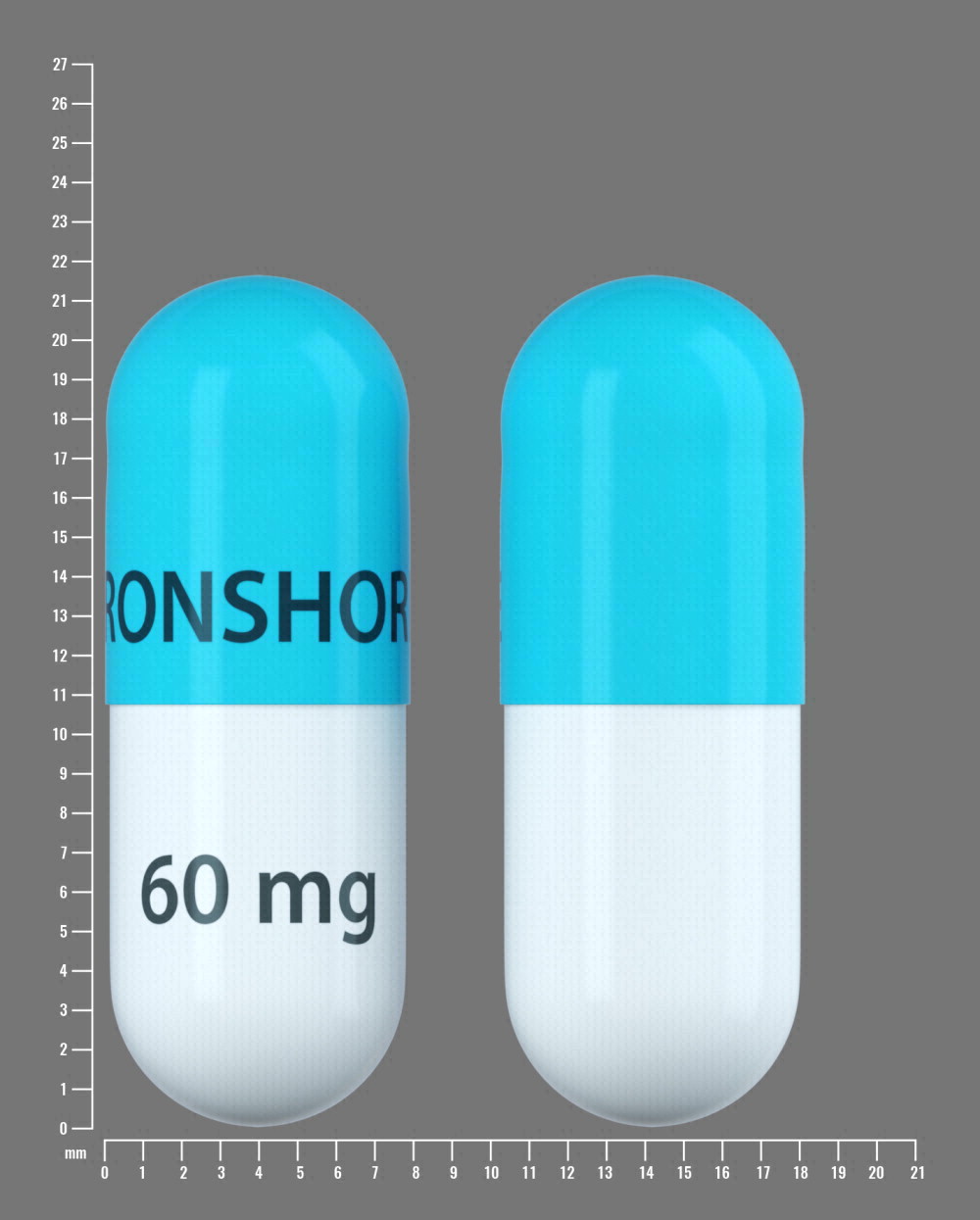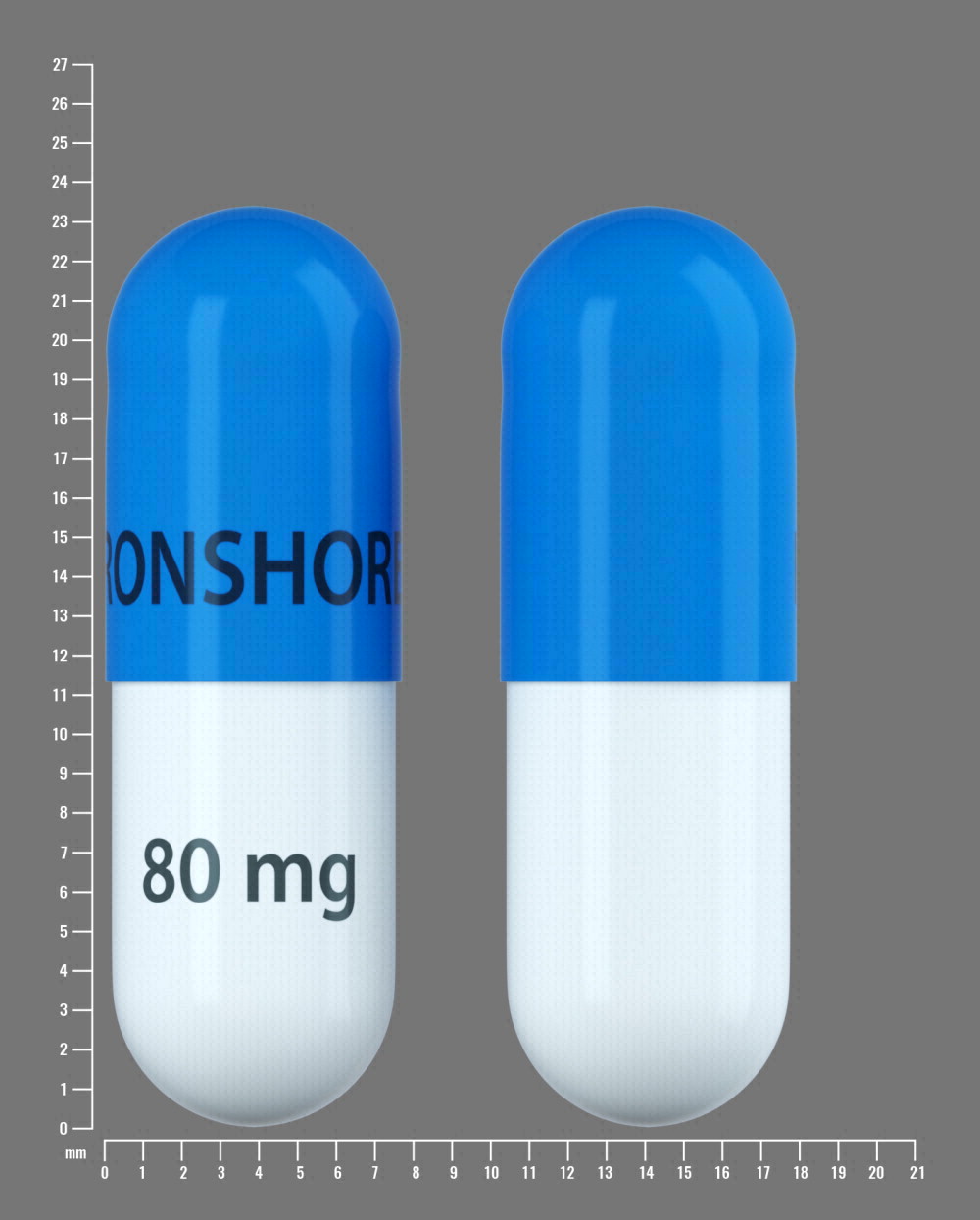 DRUG LABEL: JORNAY PM 
NDC: 71376-201 | Form: CAPSULE
Manufacturer: Ironshore Pharmaceuticals Inc.
Category: prescription | Type: HUMAN PRESCRIPTION DRUG LABEL
Date: 20251003
DEA Schedule: CII

ACTIVE INGREDIENTS: Methylphenidate Hydrochloride 20 mg/1 1
INACTIVE INGREDIENTS: microcrystalline cellulose; hypromellose 2910 (5 MPA.S); ethylcellulose (10 MPA.S); hydroxypropyl cellulose, unspecified; dibutyl sebacate; magnesium stearate; methacrylic acid - methyl methacrylate copolymer (1:2); polysorbate 80; glyceryl monostearate; talc

HIGHLIGHTS OF PRESCRIBING INFORMATION

These highlights do not include all the information needed to use JORNAY PM® safely and effectively. See full prescribing information for JORNAY PM.
JORNAY PM (methylphenidate hydrochloride) extended-release
capsules, for oral use, CII
Initial U.S. Approval: 1955

RECENT MAJOR CHANGES

Indications and Usage (1) | 09/2025
Warnings and Precautions (5.7) | 09/2025

WARNING: ABUSE, MISUSE, AND ADDICTION

See full prescribing information for complete boxed warning.

JORNAY PM has a high potential for abuse and misuse, which can lead to the development of a substance use disorder, including addiction. Misuse and abuse of CNS stimulants, including JORNAY PM, can result in overdose and death (5.1, 9.2, 10):

- Before prescribing JORNAY PM, assess each patient's risk for abuse, misuse, and addiction.
- Educate patients and their families about these risks, proper storage of the drug, and proper disposal of any unused drug.
- Throughout treatment, reassess each patient's risk and frequently monitor for signs and symptoms of abuse, misuse, and addiction.

1 INDICATIONS AND USAGE

JORNAY PM is a central nervous system (CNS) stimulant indicated for the treatment of Attention Deficit Hyperactivity Disorder (ADHD) in patients 6 years and older. (1)

Limitations of Use

The use of Jornay PM is not recommended in pediatric patients younger than 6 years of age because they had higher plasma exposure and a higher incidence of adverse reactions (e.g., weight loss) than patients 6 years and older at the same dosage (5.7, 8.4).

2 DOSAGE AND ADMINISTRATION

- JORNAY PM should be taken only in the evening. (2.2)
- Recommended starting dose for patients 6 years and above is 20 mg daily in the evening. (2.2)
- Adjust the timing of administration between 6:30 p.m. and 9:30 p.m. to optimize the tolerability and the efficacy the next morning and throughout the day.
- Dosage may be increased weekly in increments of 20 mg per day up to a maximum daily dose of 100 mg. (2.2)
- Patients are advised to take JORNAY PM consistently either with food or without food. (2.2)
- Capsules may be swallowed whole or opened and the entire contents sprinkled onto applesauce. (2.2)
- To avoid substitution errors and overdosage, do not substitute for other methylphenidate products on a milligram-per-milligram basis. (2.4)

3 DOSAGE FORMS AND STRENGTHS

- Extended-release capsules: 20 mg, 40 mg, 60 mg, 80 mg, and 100 mg. JORNAY PM exhibits both delayed-release and extended-release properties. (3)

4 CONTRAINDICATIONS

- Known hypersensitivity to methylphenidate or product components. (4)
- Concurrent treatment with a monoamine oxidase inhibitor (MAOI) or use of an MAOI within the preceding 14 days. (4)

5 WARNINGS AND PRECAUTIONS

- Risks to Patients with Serious Cardiac Disease: Avoid use in patients with known structural cardiac abnormalities, cardiomyopathy, serious cardiac arrhythmias, coronary artery disease, or other serious cardiac disease. (5.2)
- Increased Blood Pressure and Heart Rate: Monitor blood pressure and pulse. (5.3)
- Psychiatric Adverse Reactions: Prior to initiating JORNAY PM, screen patients for risk factors for developing a manic episode. If new psychotic or manic symptoms occur, consider discontinuing JORNAY PM. (5.4)
- Priapism: If abnormally sustained or frequent and painful erections occur, patients should seek immediate medical attention. (5.5)
- Peripheral Vasculopathy, including Raynaud's Phenomenon: Careful observation for digital changes is necessary during JORNAY PM treatment. Further clinical evaluation (e.g. rheumatology referral) may be appropriate for patients who develop signs or symptoms of peripheral vasculopathy (5.6)
- Long-Term Suppression of Growth in Pediatric Patients: Closely monitor growth (height and weight) in pediatric patients. Pediatric patients not growing or gaining height or weight as expected may need to have their treatment interrupted. (5.7)
- Acute Angle Closure Glaucoma: JORNAY PM-treated patients considered at risk for acute angle closure glaucoma (e.g. patients with significant hyperopia) should be evaluated by an ophthalmologist (5.8)
- Increased Intraocular Pressure (IOP) and Glaucoma: Prescribe JORNAY PM to patients with open-angle glaucoma or abnormally increased IOP only if the benefit of treatment is considered to outweigh the risk. Closely monitor patients with a history of increased IOP or open angle glaucoma. (5.9)
- Motor and Verbal Tics, and Worsening of Tourette's Syndrome: Before initiating JORNAY PM, assess the family history and clinically evaluate patients for tics or Tourette's syndrome. Regularly monitor patients for the emergence or worsening of tics or Tourette's syndrome. Discontinue treatment if clinically appropriate. (5.10)

6 ADVERSE REACTIONS

Based on accumulated data from other methylphenidate products, the most common (≥5% and twice the rate of placebo) adverse reactions for adult and pediatric patients are: appetite decreased, insomnia, nausea, vomiting, dyspepsia, abdominal pain, weight decreased, anxiety, dizziness, irritability, affect lability, tachycardia, and blood pressure increased.

Additional adverse reactions (≥5% and twice the rate of placebo) in JORNAY PM-treated pediatric patients 6 to 12 years: headache, psychomotor hyperactivity, and mood swings. (6.1)

To report SUSPECTED ADVERSE REACTIONS, contact Collegium Pharmaceutical, Inc. at 1-855-331-5615 or FDA at 1-800-FDA-1088 or www.fda.gov/medwatch.

7 DRUG INTERACTIONS

Antihypertensive Drugs: Monitor blood pressure. Adjust dosage of antihypertensive drug as needed (7.2)

FULL PRESCRIBING INFORMATION

WARNING: ABUSE, MISUSE, AND ADDICTION

JORNAY PM has a high potential for abuse and misuse, which can lead to the development of a substance use disorder, including addiction. Misuse and abuse of CNS stimulants, including JORNAY PM, can result in overdose and death [see Overdosage (10)], and this risk is increased with higher doses or unapproved methods of administration, such as snorting or injection.

Before prescribing JORNAY PM, assess each patient's risk for abuse, misuse, and addiction. Educate patients and their families about these risks, proper storage of the drug, and proper disposal of any unused drug. Throughout JORNAY PM treatment, reassess each patient's risk of abuse, misuse, and addiction and frequently monitor for signs and symptoms of abuse, misuse and addiction [see Warnings and Precautions (5.1) and Drug Abuse and Dependence (9.2)].

1 INDICATIONS AND USAGE

JORNAY PM is indicated for the treatment of Attention Deficit Hyperactivity Disorder (ADHD) in patients 6 years and older [see Clinical Studies (14)].

Limitations of Use

The use of Jornay PM is not recommended in pediatric patients younger than 6 years of age because they had higher plasma exposure and a higher incidence of adverse reactions (e.g., weight loss) than patients 6 years and older at the same dosage [see Warnings and Precautions (5.7), Use in Specific Populations (8.4)].

2 DOSAGE AND ADMINISTRATION

2.1 Pretreatment Screening

Prior to treating patients with JORNAY PM, assess:

- for the presence of cardiac disease (i.e., perform a careful history, family history of sudden death or ventricular arrhythmia, and physical exam) [see Warnings and Precautions (5.2)].
- the family history and clinically evaluate patients for motor or verbal tics or Tourette's syndrome [see Warnings and Precautions (5.10)].

2.2 Recommended Dosage

The recommended starting dosage of JORNAY PM in patients 6 years and older is 20 mg once daily orally in the evening. Do not take JORNAY PM in the morning. The dose may be titrated weekly in increments of 20 mg. A daily dosage above 100 mg has not been studied and is not recommended.

Initiate dosing at 8:00 p.m. Adjust the timing of administration between 6:30 p.m. and 9:30 p.m. to optimize the tolerability and efficacy the next morning and throughout the day. In clinical trials of patients aged 6 to 12 years, the most common dosing time (>70% of patients) was 8:00 p.m., with an allowed range between 6:30 p.m. and 9:30 p.m. Following determination of the optimal administration time, advise patients to maintain a consistent dosing time.

Advise patients to take JORNAY PM consistently, either with food or without food.

Patients who miss their dose of JORNAY PM at the regularly scheduled time should take it as soon as they remember that same evening. If a patient remembers the missed dose the following morning, they should skip the missed dose and wait until their next scheduled evening administration.

2.3 Administration Instructions

JORNAY PM may be taken whole, or the capsule may be opened, and the entire contents sprinkled onto applesauce. If the patient is using the sprinkled administration method, the sprinkled applesauce should be consumed immediately; it should not be stored. Patients should take the applesauce with sprinkled beads in its entirety without chewing. The dose of a single capsule should not be divided. The contents of the entire capsule should be taken at the same time.

2.4 Switching from Other Methylphenidate Products

If switching from other methylphenidate products, discontinue that treatment, and titrate with JORNAY PM using the titration schedule described above.

Do not substitute JORNAY PM for other methylphenidate products on a milligram-per-milligram basis because these products have different pharmacokinetic profiles from JORNAY PM and may have different methylphenidate base composition [see Description (11) and Clinical Pharmacology (12.3)].

2.5 Dosage Reduction and Discontinuation

If paradoxical aggravation of symptoms or other adverse reactions occur, reduce dosage or, if necessary, discontinue JORNAY PM. If improvement is not observed after appropriate dosage adjustment over a one-month period, discontinue JORNAY PM.

3 DOSAGE FORMS AND STRENGTHS

JORNAY PM (methylphenidate hydrochloride) extended-release capsules exhibit both delayed-release and extended-release properties and are available in the following dose strengths:

- 20 mg capsules with ivory opaque body and light green opaque cap;
- 40 mg capsules with ivory opaque body and blue-green opaque cap;
- 60 mg capsules with white opaque body and powder blue opaque cap;
- 80 mg capsules with white opaque body and light blue opaque cap; and
- 100 mg capsules with white opaque body and dark blue opaque cap.

All capsules are imprinted with the dose in black on the body and “IRONSHORE” in black on the cap, except for the 100 mg capsule, on which “IRONSHORE” is imprinted in white.

4 CONTRAINDICATIONS

JORNAY PM is contraindicated in patients:

- With a history of hypersensitivity to methylphenidate or other components of JORNAY PM. Hypersensitivity reactions such as angioedema and anaphylactic reactions have been reported in patients treated with methylphenidate products [see Adverse Reactions (6)].
- Receiving concomitant treatment with monoamine oxidase (MAO) inhibitors, or within 14 days following discontinuation of a monoamine oxidase inhibitor, because of the risk of hypertensive crisis [see Drug Interactions (7.1)].

5 WARNINGS AND PRECAUTIONS

5.1 Abuse, Misuse, and Addiction

JORNAY PM has a high potential for abuse and misuse. The use of JORNAY PM exposes individuals to the risks of abuse and misuse, which can lead to the development of a substance use disorder, including addiction. JORNAY PM can be diverted for non-medical use into illicit channels or distribution [see Drug Abuse and Dependence (9.2]. Misuse and abuse of CNS stimulants, including JORNAY PM, can result in overdose and death [see Overdosage (10)], and this risk is increased with higher doses or unapproved methods of administration, such as snorting or injection.

Before prescribing JORNAY PM, assess each patient's risk for abuse, misuse, and addiction. Educate patients and their families about these risks and proper disposal of any unused drug. Advise patients to store JORNAY PM in a safe place, preferably locked, and instruct patients to not give JORNAY PM to anyone else.

Throughout JORNAY PM treatment, reassess each patient's risk of abuse, misuse, and addiction and frequently monitor for signs and symptoms of abuse, misuse, and addiction.

5.2 Risks to Patients with Serious Cardiac Disease

Sudden death has been reported in patients with structural cardiac abnormalities or other serious cardiac disease who were treated with CNS stimulants at the recommended ADHD dosage.

Avoid JORNAY PM use in patients with known structural cardiac abnormalities, cardiomyopathy, serious cardiac arrhythmia, coronary artery disease, or other serious cardiac disease.

5.3 Increased Blood Pressure and Heart Rate

CNS stimulants may cause an increase in blood pressure (mean increase approximately 2 to 4 mmHg) and heart rate (mean increase approximately 3 to 6 bpm). Some patients may have larger increases.

Monitor all JORNAY PM-treated patients for hypertension and tachycardia.

5.4 Psychiatric Adverse Reactions

Exacerbation of Pre-existing Psychosis

CNS stimulants may exacerbate symptoms of behavior disturbance and thought disorder in patients with a pre-existing psychotic disorder.

Induction of a Manic Episode in Patients with Bipolar Disorder

CNS stimulants may induce a manic or mixed episode in patients. Prior to initiating JORNAY PM treatment, screen patients for risk factors for developing a manic episode (e.g., comorbid or history of depressive symptoms or a family history of suicide, bipolar disorder, or depression).

New Psychotic or Manic Symptoms

CNS stimulants, at the recommended dosage, may cause psychotic or manic symptoms (e.g., hallucinations, delusional thinking, or mania) in patients without a prior history of psychotic illness or mania. In a pooled analysis of multiple short-term placebo-controlled studies of CNS stimulants, psychotic or manic symptoms occurred in approximately 0.1% of CNS stimulant-treated patients, compared with 0% of placebo-treated patients. If such symptoms occur, consider discontinuing JORNAY PM.

5.5 Priapism

Prolonged and painful erections, sometimes requiring surgical intervention, have been reported with methylphenidate use in both adult and pediatric male patients. Although priapism was not reported with methylphenidate initiation, it developed after some time on methylphenidate, often subsequent to an increase in dosage. Priapism also occurred during methylphenidate withdrawal (drug holidays or during discontinuation).

JORNAY PM-treated patients who develop abnormally sustained or frequent and painful erections should seek immediate medical attention.

5.6 Peripheral Vasculopathy, including Raynaud's Phenomenon

CNS stimulants, including JORNAY PM, used to treat ADHD are associated with peripheral vasculopathy, including Raynaud's phenomenon. Signs and symptoms are usually intermittent and mild; however, sequelae have included digital ulceration and/or soft tissue breakdown. Effects of peripheral vasculopathy, including Raynaud's phenomenon, were observed in post-marketing reports and at the therapeutic dosage of CNS stimulants in all age groups throughout the course of treatment. Signs and symptoms generally improved after dosage reduction or discontinuation of the CNS stimulant.

Careful observation for digital changes is necessary during JORNAY PM treatment. Further clinical evaluation (e.g., rheumatology referral) may be appropriate for JORNAY PM-treated patients who develop signs or symptoms of peripheral vasculopathy.

5.7 Long-term Suppression of Growth in Pediatric Patients

JORNAY PM is not approved for use and is not recommended in pediatric patients below 6 years of age [see Use in Specific Populations (8.4)].

CNS stimulants have been associated with weight loss and slowing of growth rate in pediatric patients.

Careful follow-up of weight and height in pediatric patients ages 7 to 10 years who were randomized to either methylphenidate or nonmedication-treatment groups over 14 months, as well as in naturalistic subgroups of newly methylphenidate-treated and nonmedication-treated pediatric patients over 36 months (to the ages of 10 to 13 years), suggests that pediatric patients who received methylphenidate for 7 days per week throughout the year had a temporary slowing in growth rate (on average, a total of about 2 cm less growth in height and 2.7 kg less growth in weight over 3 years), without evidence of growth rebound during this development period.

Closely monitor growth (weight and height) in JORNAY PM-treated pediatric patients. Pediatric patients not growing or gaining height or weight as expected may need to have their treatment interrupted.

5.8 Acute Angle Closure Glaucoma

There have been reports of angle closure glaucoma associated with methylphenidate treatment.

Although the mechanism is not clear, JORNAY PM-treated patients considered at risk for acute angle closure glaucoma (e.g., patients with significant hyperopia) should be evaluated by an ophthalmologist.

5.9 Increased Intraocular Pressure and Glaucoma

There have been reports of an elevation of intraocular pressure (IOP) associated with methylphenidate treatment [see Adverse Reactions (6.2)].

Prescribe JORNAY PM to patients with open-angle glaucoma or abnormally increased IOP only if the benefit of treatment is considered to outweigh the risk. Closely monitor JORNAY PM-treated patients with a history of abnormally increased IOP or open angle glaucoma.

5.10 Motor and Verbal Tics, and Worsening of Tourette's Syndrome

CNS stimulants, including methylphenidate, have been associated with the onset or exacerbation of motor and verbal tics. Worsening of Tourette's syndrome has also been reported [see Adverse Reactions (6.2)].

Before initiating JORNAY PM, assess the family history and clinically evaluate patients for tics or Tourette's syndrome. Regularly monitor JORNAY PM-treated patients for the emergence or worsening of tics or Tourette's syndrome, and discontinue treatment if clinically appropriate.

6 ADVERSE REACTIONS

The following adverse reactions are discussed in more detail in other sections of the labeling:

- Abuse, Misuse, and Addiction [see Boxed Warning, Warnings and Precautions (5.1), and Drug Abuse and Dependence (9.2, 9.3)]
- Hypersensitivity to methylphenidate or other components of JORNAY PM [see Contraindications (4)]
- Hypertensive crisis when used concomitantly with monoamine oxidase inhibitors [see Contraindications (4) and Drug Interactions (7.1)]
- Risks to Patients with Serious Cardiac Disease [see Warnings and Precautions (5.2)]
- Increased Blood Pressure and Heart Rate [see Warnings and Precautions (5.3)]
- Psychiatric Adverse Reactions [see Warnings and Precautions (5.4)]
- Priapism [see Warnings and Precautions (5.5)]
- Peripheral Vasculopathy, including Raynaud's Phenomenon [see Warnings and Precautions (5.6)]
- Long-term Suppression of Growth in Pediatric Patients [see Warnings and Precautions (5.7)]
- Acute Angle Closure Glaucoma [see Warnings and Precautions (5.8)]
- Increased Intraocular Pressure and Glaucoma [see Warnings and Precautions (5.9)]
- Motor and Verbal Tics, and Worsening of Tourette's Syndrome [see Warnings and Precautions (5.10)]

6.1 Clinical Trials Experience

Because clinical trials are conducted under widely varying conditions, adverse reaction rates observed in the clinical trials of a drug cannot be directly compared with rates in the clinical trials of another drug and may not reflect the rates observed in clinical practice.

Adverse Reactions in Studies with Other Methylphenidate Products in Children, Adolescents, and Adults with ADHD

Commonly reported (≥2% of the methylphenidate group and at least twice the rate of the placebo group) adverse reactions from placebo-controlled trials of methylphenidate products include: appetite decreased, weight decreased, nausea, abdominal pain, dyspepsia, dry mouth, vomiting, insomnia, anxiety, nervousness, restlessness, affect lability, agitation, irritability, dizziness, vertigo, tremor, blurred vision, blood pressure increased, heart rate increased, tachycardia, palpitations, hyperhidrosis, and pyrexia.

Adverse Reactions in Studies with JORNAY PM in Pediatric Patients (6 to 12 years) with ADHD

The safety of JORNAY PM was evaluated in 280 patients (6 to 12 years of age) who participated in two controlled clinical studies of patients with ADHD [see Clinical Studies (14)].

Study 1, conducted in pediatric patients 6 to 12 years of age, was comprised of a 6-week open-label dose-optimization phase in which all patients received JORNAY PM (n=125; mean dose 50 mg), followed by a 1-week, double-blind controlled phase in which patients were randomized to continue JORNAY PM (n=65) or switch to placebo (n=54). During the open-label JORNAY PM treatment phase, adverse reactions reported in > 5% of patients included: any insomnia (41%), decreased appetite (27%), affect lability (22%), headache (19%), upper respiratory tract infection (17%), upper abdominal pain (9%), nausea or vomiting (9%), increased diastolic blood pressure (8%), tachycardia (7%), and irritability (6%). Three patients discontinued treatment because of adverse reactions of affect lability, panic attacks, and agitation and aggression. Because of the trial design (6-week open-label active treatment phase followed by a 1-week, randomized, double-blind, placebo-controlled withdrawal), the adverse reaction rates described in the double-blind phase are lower than expected in clinical practice. No difference occurred in the incidence of adverse reactions between JORNAY PM and placebo during the 1-week, double-blind, placebo-controlled treatment phase.

Study 2 was a 3-week, placebo-controlled study of JORNAY PM (n=81; mean dose 52mg) in pediatric patients 6 to 12 years.

Most Common Adverse Reactions (incidence of ≥ 5% and at a rate at least twice placebo): any insomnia, decreased appetite, headache, vomiting, nausea, psychomotor hyperactivity, and affect lability or mood swings.

One patient in the JORNAY PM group discontinued from the study due to mood swings.

Table 1 provides the incidence of adverse reactions reported in Study 2 (incidence of 2% or more and at least twice placebo) among pediatric patients 6 to 12 years in a 3-week clinical trial.

Table 1: Adverse Reactions that Occurred in ≥2% of JORNAY PM-treated Pediatric Patients and Greater than Placebo in a 3-Week ADHD Study (Study 2)
Body Organ System | Adverse Reaction | JORNAY PM (N=81) | Placebo (N=80)
Psychiatric disorders | Any insomnia | 33% | 9%
 | Initial insomnia | 14% | 5%
 | Middle insomnia | 11% | 4%
 | Terminal insomnia | 11% | 1%
 | Insomnia, not specified | 4% | 1%
 | Affect lability/ Mood swings | 6% | 1%
Metabolism and nutrition disorders | Decreased appetite | 19% | 4%
Nervous system disorders | Headache | 10% | 5%
 | Psychomotor hyperactivity | 5% | 1%
Cardiovascular | Blood pressure diastolic increased | 7% | 4%
Gastrointestinal disorders | Vomiting | 9% | 0%
 | Nausea | 6% | 0%
Infections and infestations | Nasopharyngitis Pharyngitis streptococcal | 3% 3% | 1% 0%
Injury, poisoning and procedural complications | Contusion | 3% | 0%
Musculoskeletal and connective tissue disorders | Back pain | 3% | 0%
Skin and subcutaneous tissue disorders | Rash | 2% | 0%

6.2 Postmarketing Experience

The following adverse reactions have been identified during postapproval use of methylphenidate products. Because these reactions are reported voluntarily from a population of uncertain size, it is not possible to reliably estimate their frequency or establish a causal relationship to drug exposure. These adverse reactions are as follows:

Blood and Lymphatic System Disorders: Pancytopenia, Thrombocytopenia, Thrombocytopenic purpura

Cardiac Disorders: Angina pectoris, Bradycardia, Extrasystole, Supraventricular tachycardia, Ventricular extrasystole

Eye Disorders: Diplopia, Increased intraocular pressure, Mydriasis, Visual impairment

General Disorders: Chest pain, Chest discomfort, Hyperpyrexia

Immune System Disorders: Hypersensitivity reactions such as Angioedema, Anaphylactic reactions, Auricular swelling, Bullous conditions, Exfoliative conditions, Urticarias, Pruritus, Rashes, Eruptions, and Exanthemas

Investigations: Alkaline phosphatase increased, Bilirubin increased, Hepatic enzyme increased, Platelet count decreased, White blood cell count abnormal, Severe hepatic injury

Musculoskeletal, Connective Tissue and Bone Disorders: Arthralgia, Myalgia, Muscle twitching, Rhabdomyolysis

Nervous System Disorders: Convulsion, Grand mal convulsion, Dyskinesia, Serotonin syndrome in combination with serotonergic drugs, Motor and Verbal Tics

Psychiatric Disorders: Disorientation, Hallucination, Hallucination auditory, Hallucination visual, Libido changes, Mania

Urogenital System: Priapism

Skin and Subcutaneous Tissue Disorders: Alopecia, Erythema

Vascular Disorders: Raynaud's phenomenon

7 DRUG INTERACTIONS

7.1 MAO Inhibitors

Do not administer JORNAY PM concomitantly with MAOIs or within 14 days after discontinuing MAOI treatment. Concomitant use of MAO inhibitors and CNS stimulants can cause hypertensive crisis. Potential outcomes include death, stroke, myocardial infarction, aortic dissection, ophthalmological complications, eclampsia, pulmonary edema, and renal failure [see Contraindications (4)].

7.2 Antihypertensive Drugs

JORNAY PM may decrease the effectiveness of drugs used to treat hypertension. Monitor blood pressure and adjust the dosage of the antihypertensive drug as needed [see Warnings and Precautions (5.3)].

7.3 Halogenated Anesthetics

Concomitant use of halogenated anesthetics and JORNAY PM may increase the risk of sudden blood pressure and heart rate increase during surgery. Monitor blood pressure and avoid use of JORNAY PM in patients being treated with anesthetics on the day of surgery.

7.4 Risperidone

The combined use of methylphenidate with risperidone when there is a change in dose of either or both medications may increase the risk of extrapyramidal symptoms (EPS). Monitor for signs of EPS.

8 USE IN SPECIFIC POPULATIONS

8.1 Pregnancy

Pregnancy Exposure Registry

There is a pregnancy exposure registry that monitors pregnancy outcomes in women exposed to JORNAY PM during pregnancy. Healthcare providers are encouraged to register patients by calling the National Pregnancy Registry for Psychostimulants at 1-866-961-2388.

Risk Summary

Published studies and postmarketing reports on methylphenidate use during pregnancy are insufficient to inform a drug-associated risk of adverse pregnancy-related outcomes [see Data]. No teratogenic effects were observed in embryo-fetal development studies with oral administration of methylphenidate to pregnant rats and rabbits during organogenesis at doses up to 2 and 9 times the maximum recommended human dose (MRHD) of 100 mg/day given to adolescents on a mg/m^2 basis, respectively. However, spina bifida was observed in rabbits at a dose 31 times the MRHD given to adolescents. A decrease in pup body weight was observed in a pre-and post-natal development study with oral administration of methylphenidate to rats throughout pregnancy and lactation at doses 3.5 times the MRHD given to adolescents [see Data].

The background risk of major birth defects and miscarriage for the indicated population is unknown. However, the background risk in the U.S. general population of major birth defects is 2% to 4% and of miscarriage is 15% to 20% of clinically recognized pregnancies.

Clinical Considerations

Fetal/Neonatal Adverse Reactions

CNS stimulant medications, such as JORNAY PM, can cause vasoconstriction and thereby decrease placental perfusion. No fetal and/or neonatal adverse reactions have been reported with the use of therapeutic doses of methylphenidate during pregnancy; however, premature delivery and low birth weight infants have been reported in amphetamine-dependent mothers.

Data

Human Data

A limited number of pregnancies have been reported in published observational studies and postmarketing reports describing methylphenidate use during pregnancy. Due to the small number of methylphenidate-exposed pregnancies with known outcomes, these data cannot definitely establish or exclude any drug-associated risk during pregnancy. Methodological limitations of these observational studies include small sample size, concomitant use of other medications, lack of detail regarding dose and duration of exposure to methylphenidate and nongeneralizability of the enrolled populations.

Animal Data

In studies conducted in rats and rabbits, methylphenidate was administered orally at doses of up to 75 and 200 mg/kg/day, respectively, during the period of organogenesis. Teratogenic effects (increased incidence of fetal spina bifida) were observed in rabbits at the highest dose, which is approximately 31 times the maximum recommended human dose (MRHD) of 100 mg/day given to adolescents on a mg/m^2 basis. The no effect level for embryo-fetal development in rabbits was 60 mg/kg/day (9 times the MRHD given to adolescents on a mg/m^2 basis). There was no evidence of specific teratogenic activity in rats, although increased incidences of fetal skeletal variations were seen at the highest dose level (6 times the MRHD given to adolescents on a mg/m^2 basis), which was also maternally toxic. The no effect level for embryo-fetal development in rats was 25 mg/kg/day (2 times the MRHD given to adolescents on a mg/m^2 basis).

8.2 Lactation

Risk Summary

Limited published literature, based on breast milk sampling from five mothers, reports that methylphenidate is present in human milk, which resulted in infant doses of 0.16% to 0.7% of the maternal weight-adjusted dosage and a milk/plasma ratio ranging between 1.1 and 2.7. There are no reports of adverse effects on the breastfed infant and no effects on milk production. However, long-term neurodevelopmental effects on infants from CNS stimulant exposure are unknown. The developmental and health benefits of breastfeeding should be considered along with the mother's clinical need for JORNAY PM and any potential adverse effects on the breastfed infant from JORNAY PM or from the underlying maternal condition.

Clinical Considerations

Monitor breastfeeding infants for adverse reactions, such as agitation, insomnia, anorexia, and reduced weight gain.

8.4 Pediatric Use

The safety and effectiveness of JORNAY PM have not been established in pediatric patients below the age of 6 years.

In studies evaluating extended-release methylphenidate products, patients 4 to <6 years of age had higher systemic methylphenidate exposures than those observed in older pediatric patients at the same dosage. Pediatric patients 4 to <6 years of age also had a higher incidence of adverse reactions, including weight loss.

The safety and effectiveness of JORNAY PM have been established in pediatric patients ages 6 to 17 years in two adequate and well-controlled clinical studies in pediatric patients 6 to 12 years, pharmacokinetic data in adults, and safety information from other methylphenidate-containing products [see Clinical Studies (14) and see Clinical Pharmacology (12.3)].

Long-Term Suppression of Growth

Growth should be monitored during treatment with stimulants, including JORNAY PM. Pediatric patients who are not growing or gaining weight as expected may need to have their treatment interrupted [see Warnings and Precautions (5.7)].

Juvenile Animal Toxicity Data

Rats treated with methylphenidate early in the postnatal period through sexual maturation demonstrated a decrease in spontaneous locomotor activity in adulthood. A deficit in acquisition of a specific learning task was observed in females only. The doses at which these findings were observed are at least 2.5 times the maximum recommended human dose (MRHD) of 100 mg/day given to children on a mg/m^2 basis.

In a study conducted in young rats, methylphenidate was administered orally at doses of up to 100 mg/kg/day for 9 weeks, starting early in the postnatal period (postnatal Day 7) and continuing through sexual maturity (postnatal week 10). When these animals were tested as adults (postnatal weeks 13-14), decreased spontaneous locomotor activity was observed in males and females previously treated with ≥ 50 mg/kg/day (approximately ≥ 2.5 times the MRHD of 100 mg/day given to children on a mg/m^2 basis), and a deficit in the acquisition of a specific learning task was seen in females exposed to the highest dose (5 times the MRHD of 100 mg/day given to children on a mg/m^2 basis). The no effect level for juvenile neurobehavioral development in rats was 5 mg/kg/day (0.25 times the MRHD of 100 mg/day given to children on a mg/m^2 basis). The clinical significance of the long-term behavioral effects observed in rats is unknown.

8.5 Geriatric Use

JORNAY PM has not been studied in patients older than 65 years of age.

9 DRUG ABUSE AND DEPENDENCE

9.1 Controlled Substance

JORNAY PM contains methylphenidate, a Schedule II controlled substance.

9.2 Abuse

JORNAY PM has a high potential for abuse and misuse which can lead to the development of a substance use disorder, including addiction [see Warnings and Precautions (5.1)]. JORNAY PM can be diverted for non-medical use into illicit channels or distribution.

Abuse is the intentional non-therapeutic use of a drug, even once, to achieve a desired psychological or physiological effect. Misuse is the intentional use, for therapeutic purposes, of a drug by an individual in a way other than prescribed by a health care provider or for whom it was not prescribed. Drug addiction is a cluster of behavioral, cognitive, and physiological phenomena that may include a strong desire to take the drug, difficulties in controlling drug use (e.g., continuing drug use despite harmful consequences, giving a higher priority to drug use than other activities and obligations), and possible tolerance or physical dependence.

Misuse and abuse of methylphenidate may cause increased heart rate, respiratory rate, or blood pressure; sweating; dilated pupils; hyperactivity; restlessness; insomnia; decreased appetite; loss of coordination; tremors; flushed skin; vomiting; and/or abdominal pain. Anxiety, psychosis, hostility, aggression, and suicidal or homicidal ideation have also been observed with CNS stimulants abuse and/or misuse. Misuse and abuse of CNS stimulants, including JORNAY PM, can result in overdose and death [see Overdosage (10)], and this risk is increased with higher doses or unapproved methods of administration, such as snorting or injection.

9.3 Dependence

Physical Dependence

JORNAY PM may produce physical dependence. Physical dependence is a state that develops as a result of physiological adaptation in response to repeated drug use, manifested by withdrawal signs and symptoms after abrupt discontinuation or a significant dose reduction of a drug.

Withdrawal signs and symptoms after abrupt discontinuation or dose reduction following prolonged use of CNS stimulants including JORNAY PM include dysphoric mood; depression; fatigue; vivid, unpleasant dreams; insomnia or hypersomnia; increased appetite; and psychomotor retardation or agitation.

Tolerance

JORNAY PM may produce tolerance. Tolerance is a physiological state characterized by a reduced response to a drug after repeated administration (i.e., a higher dose of a drug is required to produce the same effect that was once obtained at a lower dose).

10 OVERDOSAGE

Clinical Effects of Overdose

Overdose of CNS Stimulants is characterized by the following sympathomimetic effects:

- Cardiovascular effects including tachyarrhythmias, and hypertension or hypotension. Vasospasm, myocardial infarction, or aortic dissection may precipitate sudden cardiac death. Takotsubo cardiomyopathy may develop.
- CNS effects including psychomotor agitation, confusion, and hallucinations. Serotonin syndrome, seizures, cerebral vascular accidents, and coma may occur.
- Life-threatening hyperthermia (temperatures greater than 104℉) and rhabdomyolysis may develop.

Overdose Management

Consider the possibility of multiple drug ingestion. The pharmacokinetic profile of JORNAY PM should be considered when treating patients with overdose. Because methylphenidate has a large volume of distribution and is rapidly metabolized, dialysis is not useful. Consider contacting the Poison Help line (1-800-222-1222) or a medical toxicologist for additional overdose management recommendations.

11 DESCRIPTION

JORNAY PM contains methylphenidate hydrochloride, a central nervous system (CNS) stimulant.

Methylphenidate hydrochloride is a white, odorless crystalline powder. Its aqueous solutions are acidic. It is freely soluble in water and in methanol, soluble in alcohol, and slightly soluble in chloroform and in acetone. The chemical name of methylphenidate hydrochloride is d,l (racemic) methyl α-phenyl-2-piperidineacetate hydrochloride. Its molecular formula is C14H19NO2•HCl and the molecular weight is 269.77. Its structural formula is

The molecular formula of the free base is C14H19NO2 and its molecular weight is 233.31.

JORNAY PM extended-release capsules contain beads with two functional film coatings (outer delayed-release and inner extended-release) surrounding a drug core coated with methylphenidate hydrochloride. The outer, delayed-release coating delays the initial release of methylphenidate while the inner extended-release coating controls the release throughout the day. JORNAY PM is available as extended-release capsules for oral use in five strengths. Each capsule contains 20 mg, 40 mg, 60 mg, 80 mg, or 100 mg of methylphenidate hydrochloride, which is equivalent to 17.4 mg, 34.8 mg, 52.2 mg, 69.6 mg, or 87.0 mg of methylphenidate free base, respectively.

JORNAY PM capsules also contain the following inactive ingredients: dibutyl sebacate, diglycerides, ethylcellulose, hydroxypropyl cellulose, hypromellose, magnesium stearate, methacrylic acid copolymer Type B, microcrystalline cellulose, monoglycerides, polysorbate 80, and talc. The capsule shell of 20 and 40 mg strength capsules is made of FD&C Blue #1, hypromellose, titanium dioxide, yellow iron oxide, and black ink for the imprint. The capsule shell of 60 and 80 mg strength capsules is made of FD&C Blue #1, hypromellose, titanium dioxide, and black ink for the imprint. The capsule shell of 100 mg strength capsule is made of black iron oxide, FD&C Blue #1, hypromellose, red iron oxide, titanium dioxide, and black ink, and white ink for the imprint.

12 CLINICAL PHARMACOLOGY

12.1 Mechanism of Action

Methylphenidate hydrochloride is a central nervous system (CNS) stimulant. The exact mode of therapeutic action in ADHD is not known.

12.2 Pharmacodynamics

Methylphenidate is a racemic mixture comprising the d- and l-isomers. The d-isomer is more pharmacologically active than the l-isomer. Methylphenidate is thought to block the reuptake of norepinephrine and dopamine into the presynaptic neuron and increase the release of these monoamines into the extraneuronal space.

12.3 Pharmacokinetics

The pharmacokinetics of methylphenidate was dose-proportional between 20 mg and 100 mg dose level.

Absorption

The pharmacokinetics of methylphenidate after a single, 100 mg oral dose of JORNAY PM administered in the evening at 9 pm were studied in healthy adults. The initial absorption of methylphenidate into plasma is delayed such that no more than 5% of total drug is available within the first 10 hours after dosing. After the lag period, the absorption of methylphenidate occurs in a single peak with a median Tmax 14.0 hours, followed by a gradual decline throughout the rest of the day.

Figure 1: Arithmetic Mean Plasma Methylphenidate Concentrations following a Single, Oral, 100 mg Dose of JORNAY PM (Methylphenidate Hydrochloride Extended-Release Capsule) or Methylphenidate Immediate-Release Oral Product Administered in a Crossover Manner to Healthy Adult Subjects

The relative bioavailability of JORNAY PM (given once a day) compared to the same daily dose of a methylphenidate immediate-release oral product (given 3 times a day) in adults is 73.9%.

Food Effects

Compared to the fasted state, JORNAY PM taken with a high-fat meal at night exhibited similar mean AUC 0-∞, a 14% lower mean Cmax, and a median Tmax extended by approximately 2.5 hours. After JORNAY PM was taken at night, a morning meal had no effect on the pharmacokinetics of methylphenidate.

The pharmacokinetic parameters were similar when JORNAY PM was taken as a whole capsule or when sprinkled on applesauce.

Elimination

The apparent half-life of methylphenidate in adults following oral administration of JORNAY PM was approximately 5.9 hours.

Metabolism

In humans, methylphenidate is metabolized primarily by de-esterification to α-phenyl-piperidine acetic acid (PPAA). The metabolite has little pharmacologic activity.

Excretion

After oral dosing of radiolabeled methylphenidate in humans, about 90% of the radioactivity was recovered in urine. The main urinary metabolite was PPAA, accounting for approximately 80% of the dose.

Alcohol Effect:

In vitro testing showed that approximately 97% of methylphenidate was released from JORNAY PM capsules in 2 hours in the presence of 40% alcohol. The increase in methylphenidate release rate was not observed in the presence of 5 to 20% alcohol. No in vivo studies have been conducted to assess the effect of alcohol on drug exposure.

Specific populations:

Pediatric Patients

The pharmacokinetics of methylphenidate after a single, 54 mg oral dose of JORNAY PM administered in the evening at 9 pm were studied in two separate studies in adults and in children and adolescent patients with ADHD between 8 and 17 years of age. The plasma methylphenidate concentration curves were qualitatively similar in healthy adult volunteers, children 8 to 12 years, and adolescents with ADHD. Body weight dose normalized AUC and Cmax were similar in children, adolescents, and adults. However, there were differences in mean PK parameters between children, adolescents, and adults; children were exposed to higher levels of methylphenidate when provided the same dose of JORNAY PM (Cmax: children = 11.6 ng/mL, adolescents = 7.2 ng/mL, adults = 6.0 ng/mL; AUCt: children = 206 ng·hr/mL, adolescents = 106 ng·hr/mL, adults = 83.4 ng·hr/mL).

Patients with Renal Impairment:

There is no experience with the use of JORNAY PM in patients with renal insufficiency. After oral administration of radiolabeled methylphenidate in humans, methylphenidate was extensively metabolized and approximately 80% of the radioactivity was excreted in the urine in the form of PPAA. Since renal clearance is not an important route of methylphenidate clearance, renal insufficiency is expected to have little effect on the pharmacokinetics of JORNAY PM.

Patients with Hepatic Impairment

There is no experience with the use of JORNAY PM in patients with hepatic insufficiency.

13 NONCLINICAL TOXICOLOGY

13.1 Carcinogenesis, Mutagenesis, Impairment of Fertility

Carcinogenesis:

In a lifetime carcinogenicity study carried out in B6C3F1 mice, methylphenidate caused an increase in hepatocellular adenomas and, in males only, an increase in hepatoblastomas, at a daily dose of approximately 60 mg/kg/day. This dose is approximately 1.5 times the maximum recommended human dose (MRHD) of 100 mg/day given to children on a mg/m^2 basis. Hepatoblastoma is a relatively rare rodent malignant tumor type. There was no increase in total malignant hepatic tumors. The mouse strain used is sensitive to the development of hepatic tumors, and the significance of these results to humans is unknown.

Methylphenidate did not cause any increases in tumors in a lifetime carcinogenicity study carried out in F344 rats; the highest dose used was approximately 45 mg/kg/day, which is approximately 2 times the MRHD (children) on a mg/m^2 basis.

In a 24-week carcinogenicity study in the transgenic mouse strain p53+/-, which is sensitive to genotoxic carcinogens, there was no evidence of carcinogenicity. Male and female mice were fed diets containing the same concentration of methylphenidate as in the lifetime carcinogenicity study; the high-dose groups were exposed to 60 to 74 mg/kg/day of methylphenidate.

Mutagenesis:

Methylphenidate was not mutagenic in the in vitro Ames reverse mutation assay or in the in vitro mouse lymphoma cell forward mutation assay. Sister chromatid exchanges and chromosome aberrations were increased, indicative of a weak clastogenic response, in an in vitro assay in cultured Chinese Hamster Ovary (CHO) cells. Methylphenidate was negative in vivo in males and females in the mouse bone marrow micronucleus assay.

Impairment of Fertility:

Methylphenidate did not impair fertility in male or female mice that were fed diets containing the drug in an 18-week continuous breeding study. The study was conducted at doses up to 160 mg/kg/day, approximately 6-times the maximum recommended human dose of 100 mg/day given to adolescents on a mg/m^2 basis.

14 CLINICAL STUDIES

The efficacy of JORNAY PM for the treatment of ADHD was established in two clinical studies of JORNAY PM in pediatric patients 6 to 12 years of age (N = 278) who met DSM-5 criteria for ADHD inattentive, hyperactive-impulsive, or combined inattentive/hyperactive-impulsive subtypes.

Study 1 (NCT#02493777), conducted in pediatric patients 6 to 12 years of age, was comprised of a 6-week, open-label, dose-optimization phase in which all patients (n = 117) received JORNAY PM (once each evening; flexible dosing from 20 mg to 100 mg), followed by a 1-week, double-blind, placebo-controlled withdrawal phase in which patients were randomized to continue JORNAY PM (n=64; mean dose 67 mg once daily) or switch to placebo (n=53). After 1 week of double-blind treatment, patients were evaluated in an analog classroom over a 12-hour period using the Swanson, Kotkin, Agler, M-Flynn, and Pelham Scale (SKAMP), a 13-item teacher-rated scale that assesses manifestations of ADHD in a classroom setting. Possible scores range from 0 (normal/ no impairment) to 78 (maximal impairment). The primary efficacy endpoint was the model-adjusted average of all post-dose SKAMP combined scores measured during the 12-hour analog testing period from 8:00 a.m. to 8:00 p.m. The secondary efficacy measure was the morning subscale of the Parent Rating of Evening and Morning Behavior-Revised (PREMB-R AM), to measure manifestations of ADHD in the early morning. This clinician-rated scale is based on parent interview using three questions and assesses manifestations of ADHD during the early morning period. Possible scores range from 0 (no ADHD manifestations) to 9 (severe ADHD manifestations).

The primary efficacy endpoint, the model-adjusted average of all post-dose SKAMP combined scores measured during the 12-hour analog testing period, was statistically significantly better (lower) for JORNAY PM compared with placebo (Table 2). JORNAY PM showed improvement over placebo at time points (9 and 10 a.m., and 12, 2, 4, 6 and 7 p.m.) on the next day after the evening dosing. Figure 2 shows the LS mean and standard error of SKAMP combined scores at each of the individual time points from 8:00 a.m. to 8:00 p.m. The secondary efficacy endpoint, the PREMB-R AM, was also statistically significantly better (lower) for JORNAY PM versus placebo.

Study 2 (NCT#02520388) was a 3-week, multicenter, randomized, double-blind, placebo-controlled, parallel-group study in pediatric patients, 6 to 12 years of age. Patients were randomized to an oral dosage of 40, 60, or 80 mg of JORNAY PM (n=81) or placebo (n=80) once in the evening. The primary efficacy measure was the ADHD Rating Scale (ADHD-RS-IV) Total Score, measuring severity of manifestations throughout the day. Possible scores range from 0 (no ADHD manifestations) to 54 (severe symptoms of both ADHD subtypes). Normative scores range 18 to 29 in ADHD. The secondary efficacy measure was the Before School Functioning Questionnaire (BSFQ), a clinician-rated 20-item questionnaire assessing ADHD manifestations on a severity scale of 0 to 3. BSFQ is intended to assess early morning before school activities from the time the child awakens and some behaviors not specific to early morning. Possible scores range from 0 (no difficulty) to 60 (severe difficulty).

After 3 weeks of treatment, the ADHD-RS-IV total scores were statistically significantly better (lower) for JORNAY PM than placebo (Table 2). The secondary efficacy endpoint, the BSFQ, was also statistically significantly better (lower) for JORNAY PM versus placebo.

Table 2 summarizes the primary endpoint results for Study 1 and Study 2.

Table 2: Summary of Primary Efficacy Results in Pediatric Patients (6 – 12 years old) with ADHD (Studies 1 and 2)
Study Number. | Measure (Primary Endpoint) | Treatment Group (#IIT Subjects) JORNAY PM (64) | Mean Baseline Score (SD) NA | LS Mean (SE) | Placebo-subtracted Difference (95% CI)
Study 1 | SKAMP CS Average | Treatment Group (#IIT Subjects) JORNAY PM (64) | Mean Baseline Score (SD) NA |  | Placebo-subtracted Difference (95% CI)
Study 1 | SKAMP CS Average | Treatment Group (#IIT Subjects) JORNAY PM (64) | Mean Baseline Score (SD) NA | 14.8 (1.17) | -5.9 (-9.1, -2.7)
Study 1 | SKAMP CS Average | Placebo (53) | NA | 20.7 (1.22) | -5.9 (-9.1, -2.7)
Study 2 | ADHD-RS-IV | JORNAY PM (81) | 43.1 (7.33) | 24.1 (1.50) | -7.0 (-11.4, -2.7)
Study 2 | ADHD-RS-IV | Placebo (80) | 43.5 (6.84) | 31.2 (1.60) | -7.0 (-11.4, -2.7)
ITT: Intent-to-treat. SE: Standard Error. SD: Standard Deviation. CI: Confidence Interval. NA: Not Available.
CS: Combined Score (sum of items 1-13)

Figure 2: Study 1—LS Mean SKAMP Combined Score on Day after Final Treatment, as Measured in an Analogue Classroom in Pediatric Patients (6 to 12 years old) with ADHD, N=117

LS = Least Squares; CS = Combined Score (sum of items 1-13); N= Sample Size; SE = Standard Error

16 HOW SUPPLIED/STORAGE AND HANDLING

JORNAY PM (methylphenidate hydrochloride) extended-release capsules are available as follows:

20 mg Capsules – ivory opaque body and light green opaque cap (imprinted with “20 mg” in black on the body and “IRONSHORE” in black on the cap)

Bottles of 100................................................……………………………………………NDC 71376-201-03

40 mg Capsules – ivory opaque body and blue-green opaque cap (imprinted with “40 mg” in black on the body and “IRONSHORE” in black on the cap)

Bottles of 100................................................……………………………………………NDC 71376-202-03

60 mg Capsules – white opaque body and powder blue opaque cap (imprinted with “60 mg” in black on the body and “IRONSHORE” in black on the cap)

Bottles of 100................................................……………………………………………NDC 71376-203-03

80 mg Capsules – white opaque body and light blue opaque cap (imprinted with “80 mg” in black on the body and “IRONSHORE” in black on the cap)

Bottles of 100.......................................................................................................……… NDC 71376-204-03

100 mg Capsules – white opaque body and dark blue opaque cap (imprinted with “100 mg” in black on the body and “IRONSHORE” in white on the cap)

Bottles of 100...............................................……………………………………….……NDC 71376-205-03

Storage and Handling

Store at 20°C to 25°C (68°F to 77°F); excursions permitted to 15°C to 30°C (59°F to 86°F) [see USP Controlled Room Temperature]. Protect from humidity.

17 PATIENT COUNSELING INFORMATION

Advise the patient to read the FDA-approved patient labeling (Medication Guide).

Abuse, Misuse, and Addiction

Educate patients and their families about the risks of abuse, misuse, and addiction of JORNAY PM, which can lead to overdose and death, and proper disposal of any unused drug [see Warnings and Precautions (5.1), Drug Abuse and Dependence (9.2,), Overdosage (10)]. Advise patients to store JORNAY PM in a safe place, preferably locked, and instruct patients to not give JORNAY PM to anyone else.

Dosage and Administration Instructions

Advise patients that JORNAY PM is taken once daily in the evening. Advise patients that JORNAY PM should not be taken in the morning. It should be taken consistently, either with food or without food, and patients should establish a routine pattern of administration time.

For patients who take JORNAY PM sprinkled over applesauce, the contents of the entire capsule should be consumed immediately; it should not be stored. Patients should take the applesauce with sprinkled beads in its entirety without chewing. When initiating treatment with JORNAY PM, provide dosage escalation and administration instructions [see Dosage and Administration (2.3)].

Advise patients that if they forget to take JORNAY PM at their regularly scheduled time, they may take it as soon as they remember that same evening. If a patient remembers the following morning that they forgot to take their JORNAY PM dose the evening before, advise the patient to wait until their next scheduled evening administration.

Risks to Patients with Serious Cardiac Disease

Advise patients that there are potential risks to patients with serious cardiac disease, including sudden death, with JORNAY PM use. Instruct patients to contact a healthcare provider immediately if they develop symptoms such as exertional chest pain, unexplained syncope, or other symptoms suggestive of cardiac disease [see Warnings and Precautions (5.2)].

Increased Blood Pressure and Heart Rate

Advise patients that JORNAY PM can cause elevations in blood pressure and heart rate [see Warnings and Precautions (5.3)].

Psychiatric Adverse Reactions

Advise patients that JORNAY PM, at recommended doses, can cause psychotic or manic symptoms, even in patients without a prior history of psychotic symptoms or mania [see Warnings and Precautions (5.4)].

Priapism

Advise patients, caregivers, and family members of the possibility of painful or prolonged penile erections (priapism). Instruct the patient to seek immediate medical attention in the event of priapism [see Warnings and Precautions (5.5)].

Circulation Problems in Fingers and Toes [peripheral vasculopathy, including Raynaud's phenomenon]

- Instruct patients about the risk of peripheral vasculopathy, including Raynaud's phenomenon, and associated signs and symptoms: fingers or toes may feel numb, cool, painful, and/or may change from pale, to blue, to red.
- Instruct patients to report to their physician any new numbness, pain, skin color change, or sensitivity to temperature in fingers or toes.
- Instruct patients to call their physician immediately with any signs of unexplained wounds appearing on fingers or toes while taking JORNAY PM.
- Further clinical evaluation (e.g., rheumatology referral) may be appropriate for certain patients [see Warnings and Precautions (5.6)].

Suppression of Growth in Pediatric Patients

Advise patients, caregivers, and family members that JORNAY PM can cause slowing of growth and weight loss [see Warnings and Precautions (5.7)].

Increased Intraocular Pressure (IOP) and Glaucoma

Advise patients that IOP and glaucoma may occur during treatment with JORNAY PM [see Warnings and Precautions (5.9)].

Motor and Verbal Tics, and Worsening of Tourette's Syndrome

Advise patients that motor and verbal tics and worsening of Tourette's Syndrome may occur during treatment with JORNAY PM. Instruct patients to notify their healthcare provider if emergence of new tics or worsening of tics or Tourette's syndrome occurs [see Warnings and Precautions (5.10)].

Alcohol Effect

Advise patients to avoid alcohol, while taking JORNAY PM. Consumption of alcohol while taking JORNAY PM may result in a more rapid release of the dose of methylphenidate [see Clinical Pharmacology (12.3)].

Pregnancy Registry

Advise patients that there is a pregnancy exposure registry that monitors pregnancy outcomes in women exposed to JORNAY PM during pregnancy [see Use in Specific Populations (8.1)].

Packaged by:
Patheon Puerto Rico, Inc.
Manatí, Puerto Rico, 00674

Manufactured for:
Collegium Pharmaceutical, Inc.
Stoughton, MA 02072

MEDICATION GUIDE
JORNAY PM (JOR-nay)
(methylphenidate hydrochloride) extended-release capsules, CII

What is the most important information I should know about JORNAY PM?
JORNAY PM may cause serious side effects, including:
Abuse, misuse, and addiction. JORNAY PM has a high chance for abuse and misuse and may lead to substance use problems, including addiction. Misuse and abuse of JORNAY PM, other methylphenidate containing medicines, and amphetamine containing medicines, can lead to overdose and death. The risk of overdose and death is increased with higher doses of JORNAY PM or when it is used in ways that are not approved, such as snorting or injection.

- Your healthcare provider should check you or your child's risk for abuse, misuse, and addiction before starting treatment with JORNAY PM and will monitor you or your child during treatment.
- JORNAY PM may lead to physical dependence after prolonged use, even if taken as directed by your healthcare provider.
- Do not give JORNAY PM to anyone else. See “What is JORNAY PM?” for more information.
- Keep JORNAY PM in a safe place and properly dispose of unused medicine. See “How should I store JORNAY PM?” for more information.
- Tell your healthcare provider if you or your child have ever abused or been dependent on alcohol, prescription medicines, or street drugs.

- Risks for people with serious heart disease. Sudden death has happened in people who have heart defects or other serious heart disease.
  Your healthcare provider should check you or your child carefully for heart problems before starting JORNAY PM. Tell your healthcare provider if you or your child have any heart problems, heart disease, or heart defects.
  Call your healthcare provider right away or go to the nearest hospital emergency room right away if you or your child have any signs of heart problems such as chest pain, shortness of breath, or fainting during treatment with JORNAY PM.
- Increased blood pressure and heart rate.
  Your healthcare provider should check you or your child's blood pressure and heart rate regularly during treatment with JORNAY PM.
- Mental (psychiatric) problems, including:
  - new or worse behavior and thought problems
  - new or worse bipolar illness
  - new psychotic symptoms (such as hearing voices, or seeing or believing things that are not real) or new manic symptoms
  Tell your healthcare provider about any mental problems you or your child have, or about a family history of suicide, bipolar illness, or depression.
  Call your healthcare provider right away if you or your child have any new or worsening mental symptoms or problems during treatment with JORNAY PM, especially hearing voices, seeing or believing things that are not real, or new manic symptoms.

What is JORNAY PM?
JORNAY PM is a central nervous system (CNS) stimulant prescription medicine used for the treatment of Attention Deficit Hyperactivity Disorder (ADHD) in people 6 years of age and older. JORNAY PM may help increase attention and decrease impulsiveness and hyperactivity in people 6 years of age and older with ADHD.
JORNAY PM is not recommended for use in children under 6 years of age with ADHD.JORNAY PM is a federally controlled substance (CII) because it contains methylphenidate that can be a target for people who abuse prescription medicines or street drugs. Keep JORNAY PM in a safe place to protect it from theft. Never give your JORNAY PM to anyone else, because it may cause death or harm them. Selling or giving away JORNAY PM may harm others, and is against the law.

Who should not take JORNAY PM?
Do not take JORNAY PM if you or your child is:

- allergic to methylphenidate hydrochloride, or any of the ingredients in JORNAY PM. See the end of this Medication Guide for a complete list of ingredients in JORNAY PM.
- taking or has taken within the last 14 days, a medicine used to treat depression called a monoamine oxidase inhibitor (MAOI).

Before taking JORNAY PM, tell your or your child's healthcare provider about all medical conditions, including if you or your child:

- have heart problems, heart disease, heart defects, or high blood pressure
- have mental problems including psychosis, mania, bipolar illness, or depression, or have a family history of suicide, bipolar illness, or depression
- have circulation problems in fingers or toes
- have eye problems, including increased pressure in your eye, glaucoma, or problems with your close-up vision (farsightedness)
- have or had repeated movements or sounds (tics) or Tourette's syndrome, or have a family history of tics or Tourette's syndrome
- are pregnant or plan to become pregnant. It is not known whether JORNAY PM will harm your unborn baby.
  - There is a pregnancy registry for females who are exposed to JORNAY PM during pregnancy. The purpose of the registry is to collect information about the health of females exposed to JORNAY PM and their baby. If you or your child becomes pregnant during treatment with JORNAY PM, talk to your healthcare provider about registering with the National Pregnancy Registry for Psychostimulants. You can register by calling 1-866-961-2388.
- are breastfeeding or plan to breastfeed. JORNAY PM passes into breast milk. Talk to your healthcare provider about the best way to feed the baby during treatment with JORNAY PM.

Tell your healthcare provider about all of the medicines that you or your child takes, including prescription and over-the-counter medicines, vitamins, and herbal supplements.
JORNAY PM and some medicines may interact with each other and cause serious side effects. Sometimes the doses of other medicines will need to be adjusted during treatment with JORNAY PM.
Your healthcare provider will decide whether JORNAY PM can be taken with other medicines.
Especially tell your healthcare provider if you or your child takes medicine to treat depression, including MAOIs.
Know the medicines that you or your child takes. Keep a list of the medicines with you to show your healthcare provider and pharmacist when you or your child get a new medicine.
Do not start any new medicine during treatment with JORNAY PM without talking to your or your child's healthcare provider first.

How should JORNAY PM be taken?

- Take JORNAY PM exactly as prescribed by your healthcare provider.
- Your healthcare provider may change the dose and timing of the JORNAY PM dose if needed.
- Take JORNAY PM by mouth 1 time each day in the evening between 6:30 p.m. and 9:30 p.m.
- Take JORNAY PM at the same time each evening. JORNAY PM should not be taken in the morning.
- JORNAY PM can be taken with or without food, but take it the same way each time.
- JORNAY PM capsules may be swallowed whole, or if JORNAY PM capsules cannot be swallowed whole, the capsules may be opened and sprinkled onto applesauce. Make sure to sprinkle all the JORNAY PM onto the applesauce. The JORNAY PM dose should not be divided.
  - swallow all the applesauce and medicine mixture right away
  - do not chew the applesauce and medicine mixture
  - do not store the applesauce and medicine mixture
- If a dose of JORNAY PM is missed, it should be taken as soon as you remember the same evening. If you do not remember until the next morning you should not take the dose. Wait until that evening to take the next scheduled dose. A missed dose should not be taken in the morning.

If you or your child take too much JORNAY PM, call your healthcare provider or Poison Help line at 1-800-222-1222 or go to the nearest hospital emergency room right away.

What should be avoided during treatment with JORNAY PM?

- Avoid drinking alcohol during treatment with JORNAY PM. This may cause a faster release of the JORNAY PM medicine.

What are possible side effects of JORNAY PM?
JORNAY PM may cause serious side effects, including:

- See “What is the most important information I should know about JORNAY PM?”
- Painful and prolonged erections (priapism). Priapism has happened in males who take products that contain methylphenidate. If you or your child develops priapism, get medical help right away.
- Circulation problems in fingers and toes (peripheral vasculopathy, including Raynaud's phenomenon). Signs and symptoms may include:
  - fingers or toes may feel numb, cool, or painful
  - fingers or toes may change color from pale, to blue, to red
  Tell your healthcare provider if you or your child has numbness, pain, skin color change, or sensitivity to temperature in the fingers or toes.
  Call your healthcare provider right away if you or your child has any signs of unexplained wounds appearing on fingers or toes during treatment with JORNAY PM.
- Slowing of growth (height and weight) in children. Children should have their height and weight checked often during treatment with JORNAY PM. JORNAY PM treatment may be stopped if your child is not gaining weight or height.
- Eye problems (increased pressure in the eye and glaucoma). Call your healthcare provider right away if you or your child develop changes in your vision or eye pain, swelling, or redness.
- New or worsening tics or worsening Tourette's syndrome. Tell your healthcare provider if you or your child get any new or worsening tics or worsening Tourette's syndrome during treatment with JORNAY PM.

The most common side effects of methylphenidate products in children, adolescents, and adults with ADHD include:

- decreased appetite
- trouble sleeping
- nausea
- vomiting
- indigestion

- stomach pain
- weight loss
- anxiety
- dizziness

- irritability
- mood swings (affect lability)
- increased heart rate
- increased blood pressure

The most common side effects of JORNAY PM, in children age 6 to 12 with ADHD include:

- trouble sleeping
- decreased appetite
- restlessness (psychomotor hyperactivity)
- headache

- nausea
- mood swings
- vomiting

These are not all the possible side effects of JORNAY PM.
Call your doctor for medical advice about side effects. You may report side effects to FDA at 1-800-FDA-1088.

How should I store JORNAY PM?

- Store JORNAY PM at room temperature between 68°F to 77°F (20°C to 25°C).
- Store JORNAY PM in a safe place, like a locked cabinet. Protect from humidity.
- Dispose of remaining, unused, or expired JORNAY PM by a medicine take-back program at a U.S. Drug Enforcement Administration (DEA) authorized collection site. If no take-back program or DEA authorized collector is available, mix JORNAY PM with an undesirable, nontoxic substance such as dirt, cat litter, or used coffee grounds to make it less appealing to children and pets. Place the mixture in a container such as a sealed plastic bag and throw away JORNAY PM in the household trash. Visit www.fda.gov/drugdisposal for additional information on disposal of unused medicine.

Keep JORNAY PM and all medicines out of the reach of children.

General information about the safe and effective use of JORNAY PM.
Medicines are sometimes prescribed for purposes other than those listed in a Medication Guide. Do not use JORNAY PM for a condition for which it was not prescribed. Do not give JORNAY PM to other people, even if they have the same symptoms. It may harm them, and it is against the law.
You can ask your doctor or pharmacist for information about JORNAY PM that is written for healthcare professionals.

What are the ingredients in JORNAY PM?
Active Ingredient: methylphenidate hydrochloride
Inactive Ingredients: dibutyl sebacate, diglycerides, ethylcellulose, hydroxypropyl cellulose, hypromellose, magnesium stearate, methacrylic acid copolymer Type B, microcrystalline cellulose, monoglycerides, polysorbate 80, and talc.
The capsule shell of 20 and 40 mg strength capsules contains FD&C Blue #1, hypromellose, titanium dioxide, yellow iron oxide, and black ink for the imprint. The capsule shell of 60 and 80 mg strength capsules contains FD&C Blue #1, hypromellose, titanium dioxide, and black ink for the imprint. The capsule shell of 100 mg strength capsule contains black iron oxide, FD&C Blue#1, hypromellose, red iron oxide, titanium dioxide, black ink, and white ink for the imprint.
Manufactured for Collegium Pharmaceutical, Inc.
For more information about JORNAY PM go to www.jornaypm.com or call1-855-331-5615.

This Medication Guide has been approved by the U.S. Food and Drug Administration.

Revised: 09/2025

PACKAGE LABEL

Principal Display Panel - Jornay PM®20 mg Bottle Label

NDC 71376-201-03

Take Only In The Evening

Jornay PM® CII

[methylphenidate hydrochloride]

Extended-Release Capsules

20 mg

Attention Pharmacist: Dispense the accompanying
Medication Guide to each patient.

Rx Only

100 Capsules

PACKAGE LABEL

Principal Display Panel - Jornay PM®40 mg Bottle Label

NDC 71376-202-03

Take Only In The Evening

Jornay PM® CII

[methylphenidate hydrochloride]

Extended-Release Capsules

40 mg

Attention Pharmacist: Dispense the
accompanying Medication Guide to
each patient.

Rx Only

100 Capsules

PACKAGE LABEL

Principal Display Panel - Jornay PM®60 mg Bottle Label

NDC 71376-203-03

Take Only In The Evening

Jornay PM® CII

[methylphenidate hydrochloride]

Extended-Release Capsules

60 mg

Attention Pharmacist: Dispense the
accompanying Medication Guide to
each patient.

Rx Only

100 Capsules

PACKAGE LABEL

Principal Display Panel - Jornay PM®80 mg Bottle Label

NDC 71376-204-03

Take Only In The Evening

Jornay PM® CII

[methylphenidate hydrochloride]

Extended-Release Capsules

80 mg

Attention Pharmacist: Dispense the
accompanying Medication Guide to
each patient.

Rx Only

100 Capsules

PACKAGE LABEL

Principal Display Panel - Jornay PM®100 mg Bottle Label

NDC 71376-205-03

Take Only In The Evening

Jornay PM® CII

[methylphenidate hydrochloride]

Extended-Release Capsules

100 mg

Attention Pharmacist: Dispense the
accompanying Medication Guide to
each patient.

Rx Only

100 Capsules